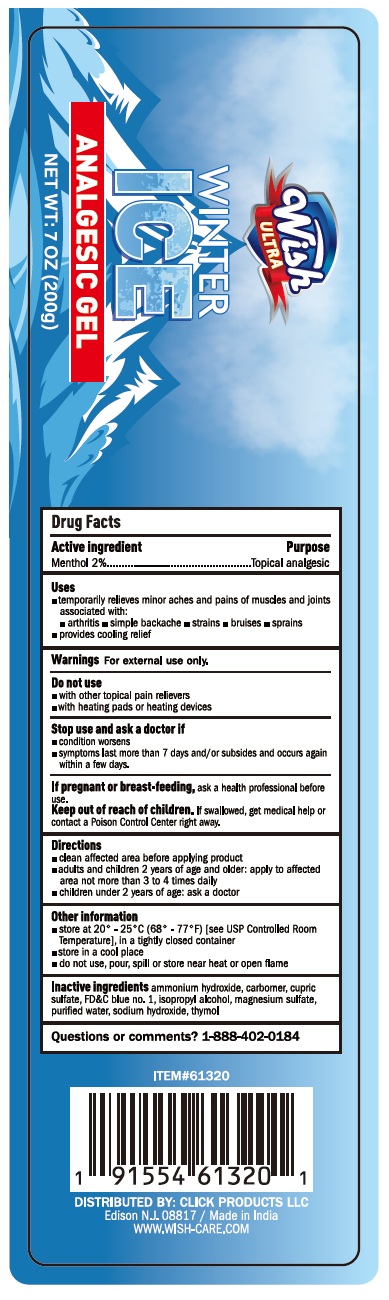 DRUG LABEL: Wish ultra winter ice
NDC: 84809-008 | Form: GEL
Manufacturer: LJ Pharma
Category: otc | Type: HUMAN OTC DRUG LABEL
Date: 20250801

ACTIVE INGREDIENTS: MENTHOL, UNSPECIFIED FORM 2 g/100 g
INACTIVE INGREDIENTS: AMMONIA; CARBOMER HOMOPOLYMER, UNSPECIFIED TYPE; CUPRIC SULFATE; FD&C BLUE NO. 1; ISOPROPYL ALCOHOL; MAGNESIUM SULFATE, UNSPECIFIED FORM; WATER; SODIUM HYDROXIDE; THYMOL

Active Ingredient Purpose

Menthol 2% Topical analgesic

Uses

Temporarily relieves minor aches and pains of muscles and joints associated with:

- Arthritis
- Simple backache
- Strains
- Bruises
- Sprains
- Provides cooling relief

Warnings

For external use only

Do not use:

- With other topical pain relievers
- With heating pads or heating devices

Stop use and ask a doctor if:

- Condition worsens
- Symptoms last more than 7 days and/or subside and occur again within a few days

If pregnant or breast-feeding: Ask a health professional before use.

Keep out of reach of children.If swallowed, get medical help or contact a Poison Control Center right away.

Directions

- Clean affected area before applying product
- Adults and children 2 years and older: Apply to affected area no more than 3 to 4 times daily
- Children under 2 years of age: Ask a doctor

Other information

- store at 20° - 25°C (68° - 77° F) [ see USP Controlled Room Temperature], in a tightly closed container
- store in a cool place
- do not use, pour, spill or store near heat or open flame

Inactive Ingredients

Ammonium hydroxide, carbomer, cupric sulfate, FD&C blue no. 1, isopropyl alcohol, magnesium sulfate, purified water, sodium hydroxide, thymol